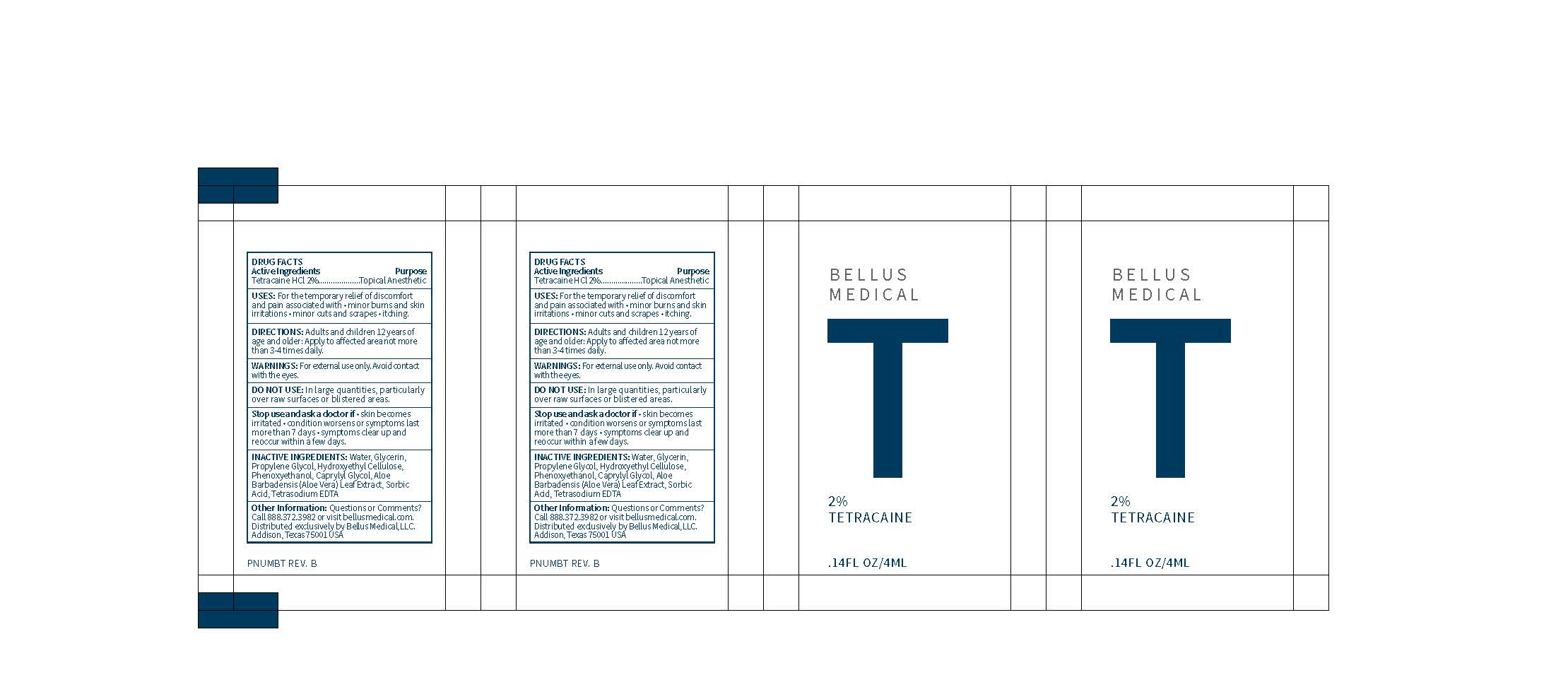 DRUG LABEL: Tetracaine
NDC: 71888-103 | Form: GEL
Manufacturer: Bellus Medical, LLC
Category: otc | Type: HUMAN OTC DRUG LABEL
Date: 20241118

ACTIVE INGREDIENTS: TETRACAINE HYDROCHLORIDE 20 mg/1000 mL
INACTIVE INGREDIENTS: HYDROXYETHYL CELLULOSE (100 MPA.S AT 2%); CAPRYLYL GLYCOL; EDETATE SODIUM; GLYCERIN; PROPYLENE GLYCOL; PHENOXYETHANOL; WATER; ALOE VERA LEAF; SORBIC ACID

2% Tetracaine Gel

ACTIVE INGREDIENT

Tetracaine HCL 2%

INACTIVE INGREDIENT

Water, Glycerin, Propylene Glycol, Hydroxyethyl Cellulose, Phenoxyethanol, Caprylyl Glycol, Aloe Barbadensis (Aloe Vera) Leaf Extract, Sorbic Acid, Tetrasodium EDTA

DOSAGE AND ADMINISTRATION

Uses : For the temporary relief of discomfort and pain associated with

- Minor burns and skin irritations
- Minor cuts and scrapes
- Itching

Directions : Adults and Children 12 years of age and older Apply to affected area not more than 3-4 times daily.

WARNINGS

Warnings : For external use only. Avoid contact with the eyes.

DO NOT USE : In large quantities, particularly over raw surfaces and blistered areas.

Stop use and ask a doctor if:

- Skin becomes irritated
- Condition worsens or symptoms last more than 7 days
- Symptoms clear up and reoccur within a few days.

PURPOSE

Topical Anesthetic

Keep out of reach of children.

INDICATIONS AND USAGE

Uses : For the temporary relief of discomfort and pain associated with

- Minor burns and skin irritations
- Minor cuts and scrapes
- Itching

Directions : Adults and Children 12 years of age and older Apply to affected area not more than 3-4 times daily.